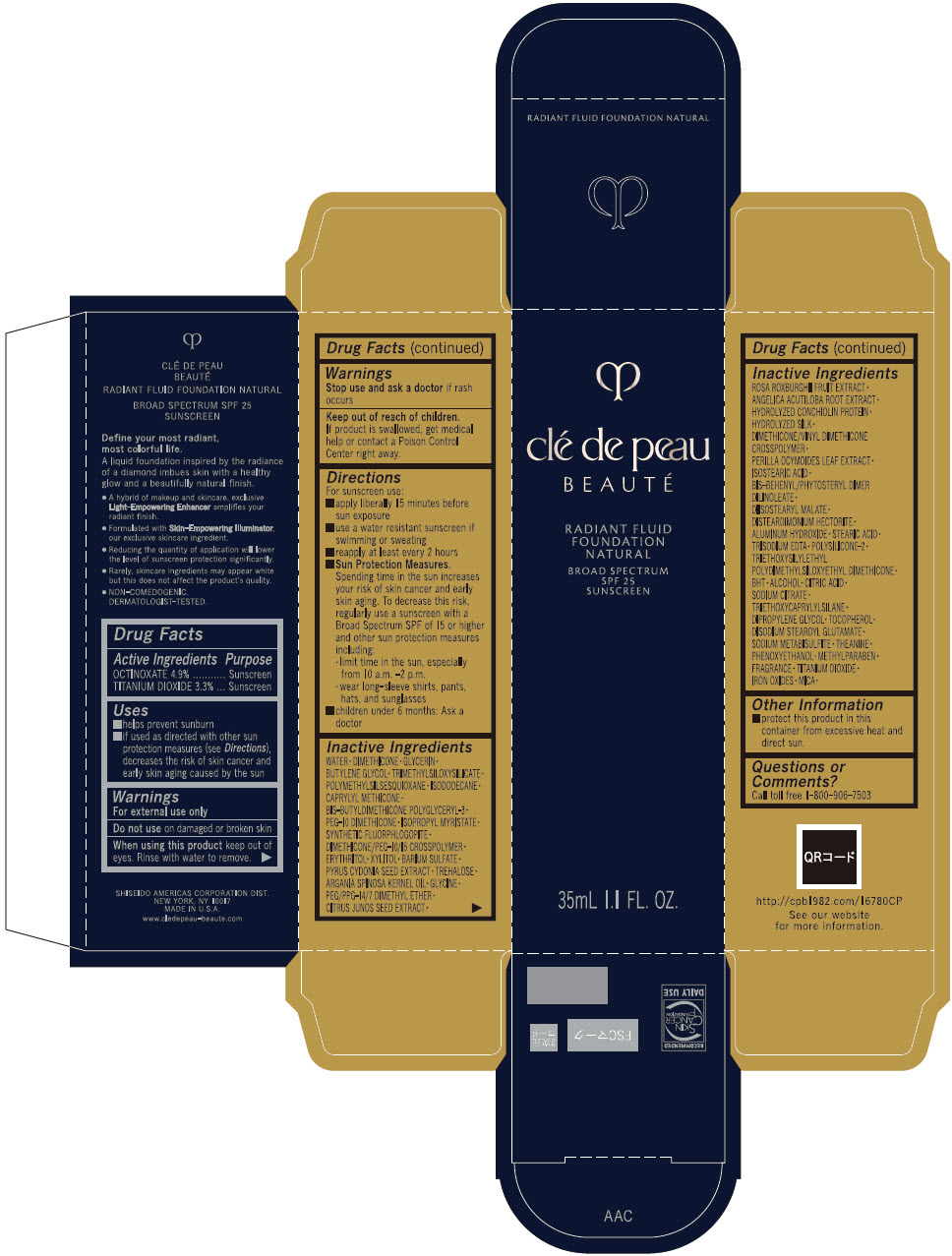 DRUG LABEL: cle de peau BEAUTE RADIANT FLUID FOUNDATION NATURAL
NDC: 58411-909 | Form: EMULSION
Manufacturer: SHISEIDO AMERICAS CORPORATION
Category: otc | Type: HUMAN OTC DRUG LABEL
Date: 20260209

ACTIVE INGREDIENTS: OCTINOXATE 1.715 g/35 mL; TITANIUM DIOXIDE 1.155 g/35 mL
INACTIVE INGREDIENTS: PEG/PPG-14/7 DIMETHYL ETHER; CITRUS JUNOS SEED; ROSA ROXBURGHII FRUIT; ANGELICA ACUTILOBA ROOT; HYDROLYZED CAPRA HIRCUS HAIR PROTEIN (ENZYMATIC; 4000 MW); HYDROLYZED SHEEP WOOL KERATIN (200 MW); DIMETHICONE/VINYL DIMETHICONE CROSSPOLYMER (HARD PARTICLE); PERILLA FRUTESCENS LEAF; ISOSTEARIC ACID; BEHENYL PHOSPHATE; DIISOSTEARYL MALATE; DISTEARDIMONIUM HECTORITE; ALUMINUM HYDROXIDE; STEARIC ACID; EDETATE TRISODIUM; POLYSILICONE-15; TRIETHOXYSILYLETHYL POLYDIMETHYLSILOXYETHYL HEXYL DIMETHICONE; BUTYLATED HYDROXYTOLUENE; ALCOHOL; CITRIC ACID ACETATE; SODIUM CITRATE, UNSPECIFIED FORM; TRIETHOXYCAPRYLYLSILANE; DIPROPYLENE GLYCOL; TOCOPHEROL; DISODIUM STEAROYL GLUTAMATE; SODIUM METABISULFITE; THEANINE; PHENOXYETHANOL; METHYLPARABEN; FRAGRANCE 13576; BROWN IRON OXIDE; MICA; WATER; DIMETHICONE; GLYCERIN; BUTYLENE GLYCOL; TRIMETHYLSILOXYSILICATE (M/Q 0.6-0.8); POLYMETHYLSILSESQUIOXANE (11 MICRONS); ISODODECANE; CAPRYLYL TRISILOXANE; BIS(BUTYLAMINO)DIMETHYLSILANE; PEG-10 DIMETHICONE (200 CST); ISOPROPYL MYRISTATE; MAGNESIUM POTASSIUM ALUMINOSILICATE FLUORIDE; DIMETHICONE/PEG-10/15 CROSSPOLYMER; ERYTHRIN; XYLITOL; BARIUM SULFATE; CYDONIA OBLONGA SEED; TREHALOSE; ARGAN OIL; GLYCINE

clé de peau BEAUTÉ RADIANT FLUID FOUNDATION NATURAL

Drug Facts

ACTIVE INGREDIENT

Active ingredients | Purpose
OCTINOXATE 4.9% | Sunscreen
TITANIUM DIOXIDE 3.3% | Sunscreen

Uses

- helps prevent sunburn
- if used as directed with other sun protection measures (see Directions), decreases the risk of skin cancer and early skin aging caused by the sun

Warnings

For external use only

Do not useon damaged or broken skin

WHEN USING

When using this productkeep out of eyes. Rinse with water to remove.

Stop use and ask a doctorif rash occurs

Keep out of reach of children.If product is swallowed, get medical help or contact a Poison Control Center right away.

Directions

For sunscreen use:

- apply liberally 15 minutes before sun exposure
- use a water resistant sunscreen if swimming or sweating
- reapply at least every 2 hours
- Sun Protection Measures. Spending time in the sun increases your risk of skin cancer and early skin aging. To decrease this risk, regularly use a sunscreen with a Broad Spectrum SPF of 15 or higher and other sun protection measures including:
  - limit time in the sun, especially from 10 a.m. – 2 p.m.
  - wear long-sleeve shirts, pants, hats, and sunglasses
- children under 6 months: Ask a doctor

Inactive Ingredients

WATER･DIMETHICONE･GLYCERIN･BUTYLENE GLYCOL･TRIMETHYLSILOXYSILICATE･POLYMETHYLSILSESQUIOXANE･ISODODECANE･CAPRYLYL METHICONE･BIS-BUTYLDIMETHICONE POLYGLYCERYL-3･PEG-10 DIMETHICONE･ISOPROPYL MYRISTATE･SYNTHETIC FLUORPHLOGOPITE･DIMETHICONE/PEG-10/15 CROSSPOLYMER･ERYTHRITOL･XYLITOL･BARIUM SULFATE･PYRUS CYDONIA SEED EXTRACT･TREHALOSE･ARGANIA SPINOSA KERNEL OIL･GLYCINE･PEG/PPG-14/7 DIMETHYL ETHER･CITRUS JUNOS SEED EXTRACT･ROSA ROXBURGHII FRUIT EXTRACT･ANGELICA ACUTILOBA ROOT EXTRACT･HYDROLYZED CONCHIOLIN PROTEIN･HYDROLYZED SILK･DIMETHICONE/VINYL DIMETHICONE CROSSPOLYMER･PERILLA OCYMOIDES LEAF EXTRACT･ISOSTEARIC ACID･BIS-BEHENYL/PHYTOSTERYL DIMER DILINOLEATE･DIISOSTEARYL MALATE･DISTEARDIMONIUM HECTORITE･ALUMINUM HYDROXIDE･STEARIC ACID･TRISODIUM EDTA･POLYSILICONE-2･TRIETHOXYSILYLETHYL POLYDIMETHYLSILOXYETHYL DIMETHICONE･BHT･ALCOHOL･CITRIC ACID･SODIUM CITRATE･TRIETHOXYCAPRYLYLSILANE･DIPROPYLENE GLYCOL･TOCOPHEROL･DISODIUM STEAROYL GLUTAMATE･SODIUM METABISULFITE･THEANINE･PHENOXYETHANOL･METHYLPARABEN･FRAGRANCE･TITANIUM DIOXIDE･IRON OXIDES･MICA･

Other information

- protect this product in this container from excessive heat and direct sun.

Questions or Comments?

Call toll free 1-800-906-7503

PRINCIPAL DISPLAY PANEL - 35 mL Vial Carton - BF10

clé de peau
BEAUTÉ

RADIANT FLUID
FOUNDATION
NATURAL

BROAD SPECTRUM
SPF 25
SUNSCREEN

35mL 1.1 FL. OZ.

PRINCIPAL DISPLAY PANEL - 35 mL Vial Carton - O80

clé de peau
BEAUTÉ

RADIANT FLUID
FOUNDATION
NATURAL

BROAD SPECTRUM
SPF 25
SUNSCREEN

35mL 1.1 FL. OZ.

PRINCIPAL DISPLAY PANEL - 35 mL Vial Carton - O90

clé de peau
BEAUTÉ

RADIANT FLUID
FOUNDATION
NATURAL

BROAD SPECTRUM
SPF 25
SUNSCREEN

35mL 1.1 FL. OZ.

PRINCIPAL DISPLAY PANEL - 35 mL Vial Carton - B50

clé de peau
BEAUTÉ

RADIANT FLUID
FOUNDATION
NATURAL

BROAD SPECTRUM
SPF 25
SUNSCREEN

35mL 1.1 FL. OZ.

PRINCIPAL DISPLAY PANEL - 35 mL Vial Carton - B60

clé de peau
BEAUTÉ

RADIANT FLUID
FOUNDATION
NATURAL

BROAD SPECTRUM
SPF 25
SUNSCREEN

35mL 1.1 FL. OZ.

PRINCIPAL DISPLAY PANEL - 35 mL Vial Carton - B80

clé de peau
BEAUTÉ

RADIANT FLUID
FOUNDATION
NATURAL

BROAD SPECTRUM
SPF 25
SUNSCREEN

35mL 1.1 FL. OZ.

PRINCIPAL DISPLAY PANEL - 35 mL Vial Carton - B10

clé de peau
BEAUTÉ

RADIANT FLUID
FOUNDATION
NATURAL

BROAD SPECTRUM
SPF 25
SUNSCREEN

35mL 1.1 FL. OZ.

PRINCIPAL DISPLAY PANEL - 35 mL Vial Carton - B100

clé de peau
BEAUTÉ

RADIANT FLUID
FOUNDATION
NATURAL

BROAD SPECTRUM
SPF 25
SUNSCREEN

35mL 1.1 FL. OZ.

PRINCIPAL DISPLAY PANEL - 35 mL Vial Carton - B20

clé de peau
BEAUTÉ

RADIANT FLUID
FOUNDATION
NATURAL

BROAD SPECTRUM
SPF 25
SUNSCREEN

35mL 1.1 FL. OZ.

PRINCIPAL DISPLAY PANEL - 35 mL Vial Carton - B30

clé de peau
BEAUTÉ

RADIANT FLUID
FOUNDATION
NATURAL

BROAD SPECTRUM
SPF 25
SUNSCREEN

35mL 1.1 FL. OZ.

PRINCIPAL DISPLAY PANEL - 35 mL Vial Carton - B40

clé de peau
BEAUTÉ

RADIANT FLUID
FOUNDATION
NATURAL

BROAD SPECTRUM
SPF 25
SUNSCREEN

35mL 1.1 FL. OZ.

PRINCIPAL DISPLAY PANEL - 35 mL Vial Carton - B70

clé de peau
BEAUTÉ

RADIANT FLUID
FOUNDATION
NATURAL

BROAD SPECTRUM
SPF 25
SUNSCREEN

35mL 1.1 FL. OZ.

PRINCIPAL DISPLAY PANEL - 35 mL Vial Carton - B90

clé de peau
BEAUTÉ

RADIANT FLUID
FOUNDATION
NATURAL

BROAD SPECTRUM
SPF 25
SUNSCREEN

35mL 1.1 FL. OZ.

PRINCIPAL DISPLAY PANEL - 35 mL Vial Carton - BF50

clé de peau
BEAUTÉ

RADIANT FLUID
FOUNDATION
NATURAL

BROAD SPECTRUM
SPF 25
SUNSCREEN

35mL 1.1 FL. OZ.

PRINCIPAL DISPLAY PANEL - 35 mL Vial Carton - BF60

clé de peau
BEAUTÉ

RADIANT FLUID
FOUNDATION
NATURAL

BROAD SPECTRUM
SPF 25
SUNSCREEN

35mL 1.1 FL. OZ.

PRINCIPAL DISPLAY PANEL - 35 mL Vial Carton - I10

clé de peau
BEAUTÉ

RADIANT FLUID
FOUNDATION
NATURAL

BROAD SPECTRUM
SPF 25
SUNSCREEN

35mL 1.1 FL. OZ.

PRINCIPAL DISPLAY PANEL - 35 mL Vial Carton - O10

clé de peau
BEAUTÉ

RADIANT FLUID
FOUNDATION
NATURAL

BROAD SPECTRUM
SPF 25
SUNSCREEN

35mL 1.1 FL. OZ.

PRINCIPAL DISPLAY PANEL - 35 mL Vial Carton - O100

clé de peau
BEAUTÉ

RADIANT FLUID
FOUNDATION
NATURAL

BROAD SPECTRUM
SPF 25
SUNSCREEN

35mL 1.1 FL. OZ.

PRINCIPAL DISPLAY PANEL - 35 mL Vial Carton - O20

clé de peau
BEAUTÉ

RADIANT FLUID
FOUNDATION
NATURAL

BROAD SPECTRUM
SPF 25
SUNSCREEN

35mL 1.1 FL. OZ.

PRINCIPAL DISPLAY PANEL - 35 mL Vial Carton - O30

clé de peau
BEAUTÉ

RADIANT FLUID
FOUNDATION
NATURAL

BROAD SPECTRUM
SPF 25
SUNSCREEN

35mL 1.1 FL. OZ.

PRINCIPAL DISPLAY PANEL - 35 mL Vial Carton - O40

clé de peau
BEAUTÉ

RADIANT FLUID
FOUNDATION
NATURAL

BROAD SPECTRUM
SPF 25
SUNSCREEN

35mL 1.1 FL. OZ.

PRINCIPAL DISPLAY PANEL - 35 mL Vial Carton - O50

clé de peau
BEAUTÉ

RADIANT FLUID
FOUNDATION
NATURAL

BROAD SPECTRUM
SPF 25
SUNSCREEN

35mL 1.1 FL. OZ.

PRINCIPAL DISPLAY PANEL - 35 mL Vial Carton - O60

clé de peau
BEAUTÉ

RADIANT FLUID
FOUNDATION
NATURAL

BROAD SPECTRUM
SPF 25
SUNSCREEN

35mL 1.1 FL. OZ.

PRINCIPAL DISPLAY PANEL - 35 mL Vial Carton - O70

clé de peau
BEAUTÉ

RADIANT FLUID
FOUNDATION
NATURAL

BROAD SPECTRUM
SPF 25
SUNSCREEN

35mL 1.1 FL. OZ.